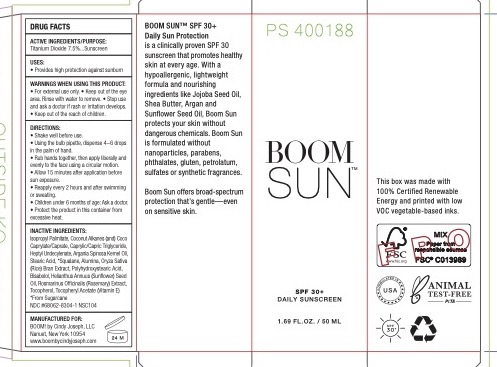 DRUG LABEL: Boom Sun SPF 30
NDC: 68062-9910 | Form: LOTION
Manufacturer: Spa de Soleil
Category: otc | Type: HUMAN OTC DRUG LABEL
Date: 20221226

ACTIVE INGREDIENTS: TITANIUM DIOXIDE 3.75 mg/50 mL
INACTIVE INGREDIENTS: TOCOPHEROL; LEVOMENOL; HELIANTHUS ANNUUS SEED WAX; ROSMARINUS OFFICINALIS FLOWERING TOP OIL; SQUALANE; ARGANIA SPINOSA SEED; ISOPROPYL PALMITATE; COCONUT ALKANES; STEARIC ACID; COCO-CAPRYLATE/CAPRATE; HEPTYL UNDECYLENATE; ALUMINUM OXIDE; ORYZA SATIVA WHOLE; POLYHYDROXYSTEARIC ACID (2300 MW); ALPHA-TOCOPHEROL ACETATE

Boom Sun SPF 30

Active Ingredients

Titanium Dioxide 7.5%

Purpose

Sunscreen

Warnings

Warnings When using this product

- keep out of the eye area
- rinse with water to remove
- stop use and ask a doctor if rash or irritation develops
- for external use onlyl
- keep out of reach of children

Keep out of the reach of children.

Directions

Shake well before use

Using the bulb pipette, dispense 4-6 drops in the palm of the hand.
Rub hands together, then apply liberally and evenly to the face using a circular motion.
Allow 15 minutes after application before sun exposure.
Reapply every 2 hours and after swimming or sweating.
Children under 6 months of age: Ask a doctor.
Protect the product in this container from excessive heat.

Inactive Ingredients

Isopropyl Palmitate, Coconut Alkanes (and) Coco Caprylate/Caprate, Caprylic/Capric Triglyceride, Heptyl Undecylenate, Argania Spinosa Kernel Oil, Stearic Acid, *Squalane, Alumina, Oryza Sativa (Rice) Bran Extract, Polyhydroxystearic Acid, Bisabolol, Helianthus Annuus (Sunflower) Seed Oil, Rosmarinus Officinalis (Rosemary) Extract, Tocopherol, Tocopheryl Acetate (Vitamin E)
* From Sugarcane